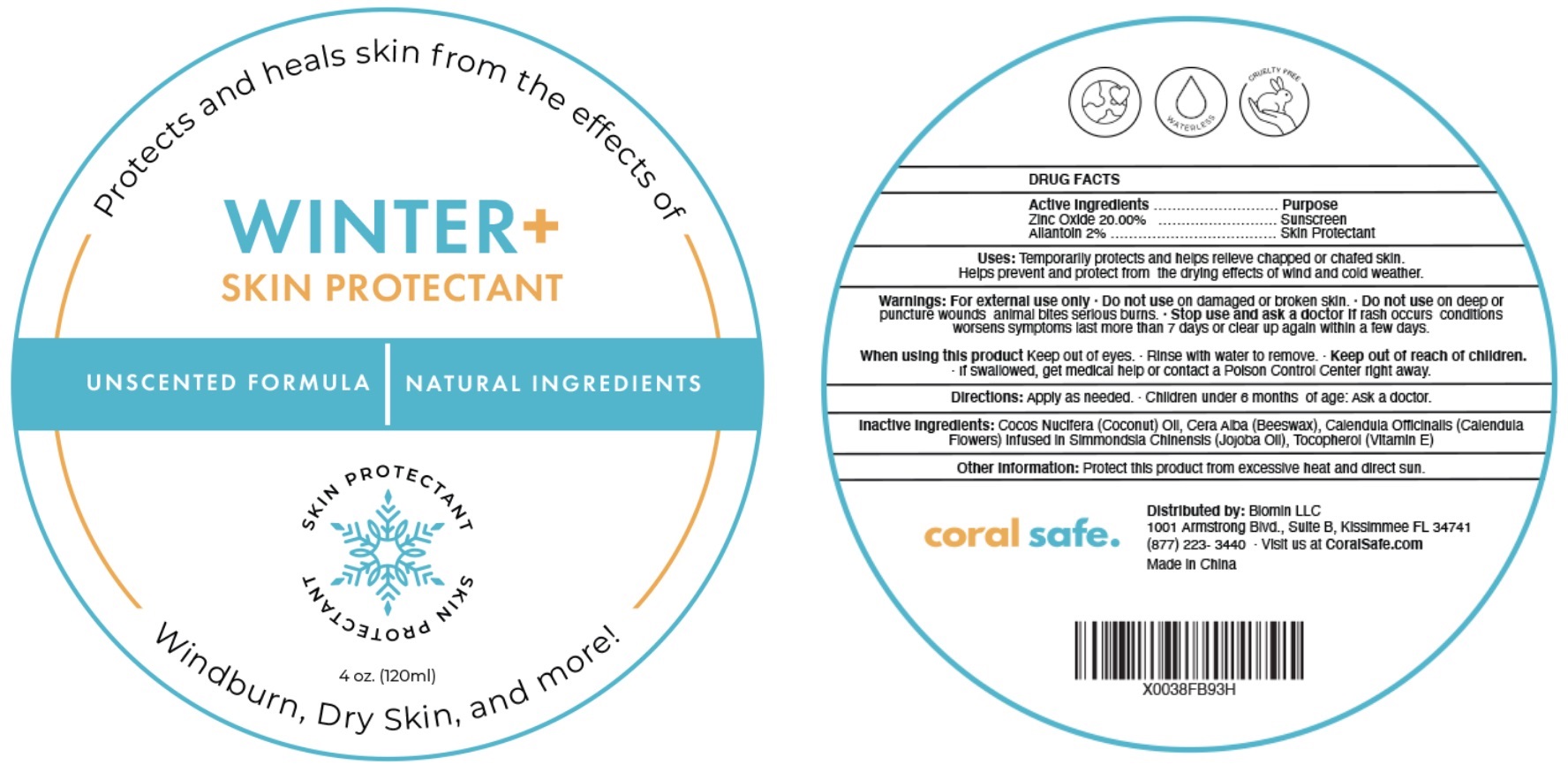 DRUG LABEL: Winter Skin Protectant
NDC: 82177-001 | Form: OINTMENT
Manufacturer: Biomin LLC.
Category: otc | Type: HUMAN OTC DRUG LABEL
Date: 20220602

ACTIVE INGREDIENTS: ZINC OXIDE 200 mg/1 mL; ALLANTOIN 20 mg/1 mL
INACTIVE INGREDIENTS: COCONUT OIL; YELLOW WAX; CALENDULA OFFICINALIS FLOWER; JOJOBA OIL; TOCOPHEROL

Winter + Skin Protectant

Active Ingredients

Zinc Oxide 20.00%

Allantoin 2%

Purpose

Sunscreen

Skin Protectant

Uses:

Temporarily protects and helps relieve chapped or chafed skin. Helps prevent and protect from the drying effects of wind and cold weather.

Warnings:

For external use only.

Do not use

- on damaged or broken skin.
- Do not use deep or puncture wounds animal bites serious burns.

Stop use and ask a doctor

- If rash occurs conditions worsens symptoms last more than 7 days or clear up again within a few days.

When using this product

- Keep out of eyes.
- Rinse with water to remove.

Keep out of reach of children.

- If swallowed, get medical help or contact a Poison Control Center right away.

Directions:

- Apply as needed.
- Children under 6 months of age: Ask a doctor.

Inactive Ingredients:

Cocos Nucifera (Coconut) Oil, Cera Alba (Beeswax), Calendula Officinalis (Calendula Flower) Infused in Simmondsia Chinensis (Jojoba Oil), Tocopherol (Vitamin E)

Other Information:

Protect this product from excessive heat and direct sun.